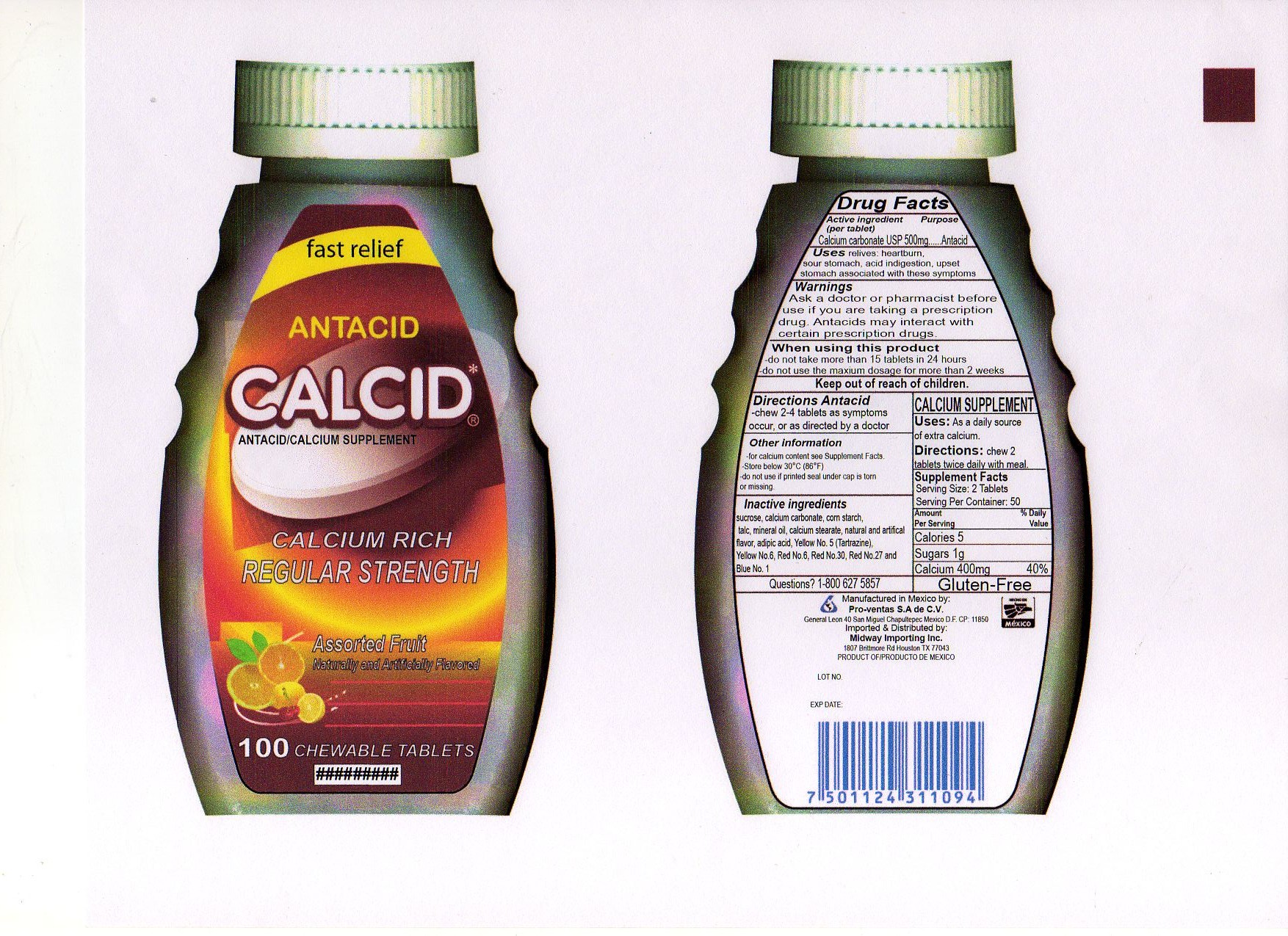 DRUG LABEL: CALCID
NDC: 24202-002 | Form: TABLET, CHEWABLE
Manufacturer: Pro-ventas S.A. de C.V.
Category: otc | Type: HUMAN OTC DRUG LABEL
Date: 20111217

ACTIVE INGREDIENTS: CALCIUM CARBONATE 500 mg/1 1
INACTIVE INGREDIENTS: SUCROSE; STARCH, CORN; TALC; MINERAL OIL; CALCIUM STEARATE; ADIPIC ACID; FD&C YELLOW NO. 5; FD&C YELLOW NO. 6; D&C RED NO. 6; D&C RED NO. 30; D&C RED NO. 27; FD&C BLUE NO. 1

Drug Facts

Active Ingredient (per tablet)
Calcium carbonate USP 500 mg

Purpose
Antacid

INDICATIONS AND USAGE

Uses relieves: heartburn, sour stomach, acid indigestion, upset stomach associated with these symptoms

Warnings
Ask a doctor or pharmacist before use if you are taking a prescription drug. Antacids may interact with certain prescription drugs

When using this product
-do not take more than 15 tablets in 24 hours
-do not use the maximum dosage for more than 2 weeks

Keep out of reach of children

DOSAGE AND ADMINISTRATION

Directions Antacid
-chew 2-4 tablets as symptoms occur or as directed by a doctor

Other information
- for calcium content see Supplement Facts.
- Store below30°C (86°F)
- do not use if printed seal under cap is torn or missing
CALCIUM SUPPLEMENT
Uses: As a daily source of extra calcium
Directions: chew 2 tablets twice daily with meal
Supplement Facts
Serving Size: 2 Tablets
Servings Per Container: 50
Amount %Daily
Per Serving Value
Calories 5
Sugars 1g
Calcium 400mg 40%

Inactive Ingredients
sucrose, calcium carbonate, corn starch, talc, mineral oil, calcium sterate, natural flavor and artificial flavor, adpic acid, Yellow No. 5, Yellow No. 6, Red No. 6, Red No. 30, Red No. 27 and Blue No. 1

Questions? 1-877 2198302

Package Label